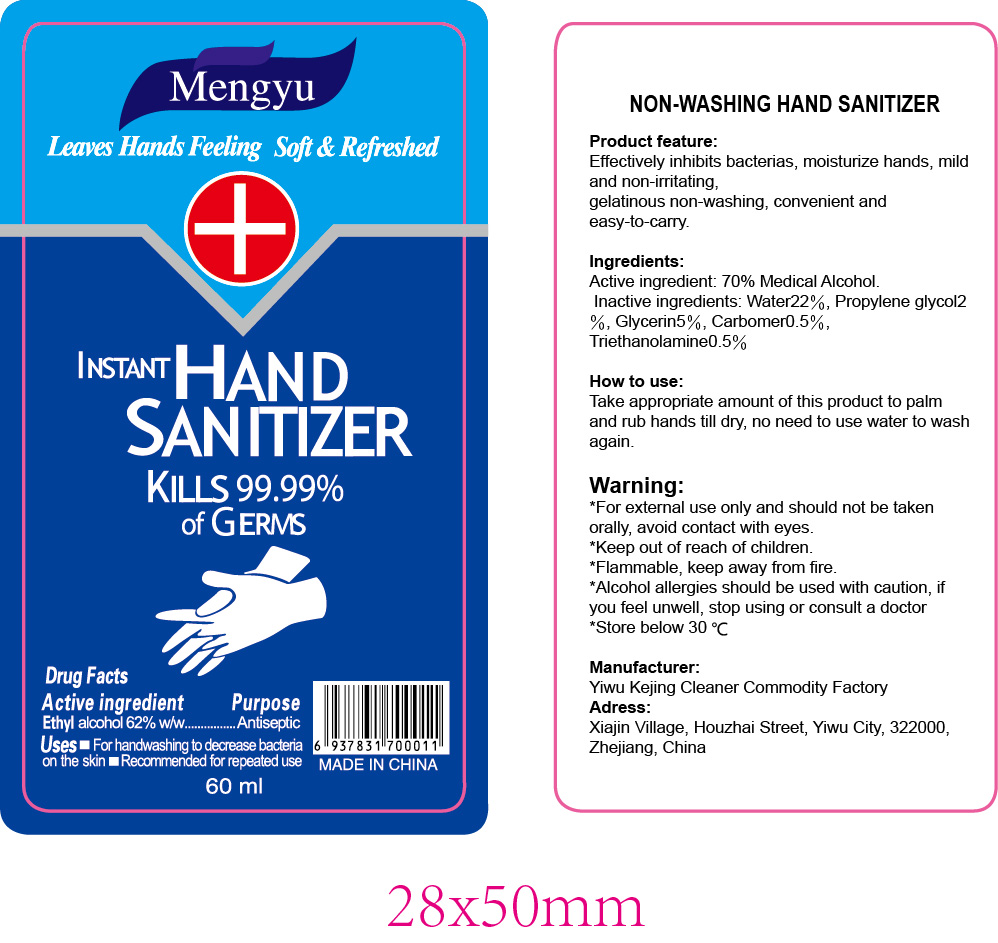 DRUG LABEL: NON-WASHING HAND SANITIZER
NDC: 52687-001 | Form: LIQUID
Manufacturer: Yiwu Kejing Cleaning Products Factory
Category: otc | Type: HUMAN OTC DRUG LABEL
Date: 20200324

ACTIVE INGREDIENTS: ALCOHOL 42 mL/60 mL
INACTIVE INGREDIENTS: CARBOMER HOMOPOLYMER, UNSPECIFIED TYPE; TROLAMINE; WATER; PROPYLENE GLYCOL; GLYCERIN

DOSAGE AND ADMINISTRATION

Effectively inhibits bacterias, moisturize hands, mild and non-irritating, gelatinous non-washing, convenient and easy-to-carry.

keep out of reach of children section

WARNINGS

*For external use only and should not be taken orally, avoid contact with eyes.

*Keep out of reach of children.

*Flammable, keep away from fire.

*Alcohol allergies should be used with caution, if you feel unwell, stop using or consult a doctor.

*Store below 30°C.

PURPOSE

Disinfection
Sterilization
No Rinseing

ACTIVE INGREDIENT

70% Medical Alcohol

INACTIVE INGREDIENT

Water 22%, Propylene glycol 2%, Glycerin 5%, Carbomer 0.5%，Triethanolamine 0.5%

INDICATIONS AND USAGE

Take appropriate amount of this product to palm and rub hands till dry, no need to use water to wash again.